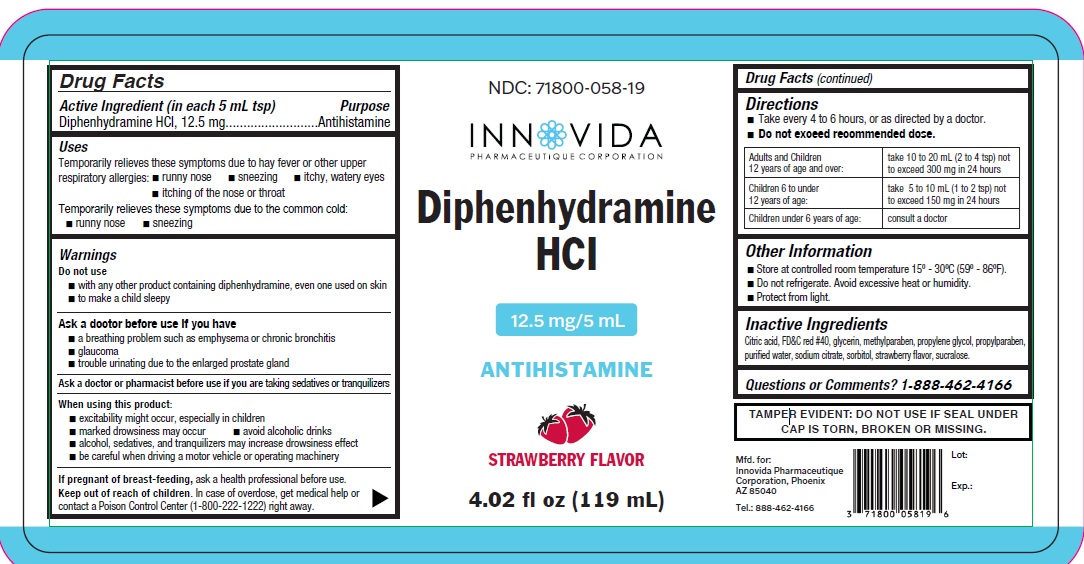 DRUG LABEL: Diphenhydramine HCL STRAWBERRY FLAVOR
NDC: 71800-058 | Form: SOLUTION
Manufacturer: Innovida Pharmaeutique Corporation
Category: otc | Type: HUMAN OTC DRUG LABEL
Date: 20250604

ACTIVE INGREDIENTS: DIPHENHYDRAMINE HYDROCHLORIDE 12.5 mg/5 mL
INACTIVE INGREDIENTS: CITRIC ACID; FD&C RED NO. 40; GLYCERIN; METHYLPARABEN; PROPYLENE GLYCOL; PROPYLPARABEN; WATER; SODIUM CITRATE; SORBITOL; SUCRALOSE; STRAWBERRY

Active Ingredient (in each 5mL tsp)

Diphenhydramine HCl, 12.5 mg

Purpose

Antihistamine

Warnings

Do not use

- with any other product containing diphenhydramine, even one used on skin
- to make a child sleepy

Ask a doctor before use if you have

- a breathing problem such as emphysema or chronic bronchitis
- glaucoma
- trouble urinating due to the enlarged prostate gland

Ask a doctor or pharmacist before use if you are takingsedatives or tranquilizers

When using this product:

- excitability might occur, especially in children
- marked drowsiness may occur
- avoid alcoholic drinks
- alcohol, sedatives, and tranquilizers may increase drowsiness effect
- be careful when driving a motor vehicle or operating machinery

If pregnant of breast-feeding, ask a health professional before use.

Keep out of reach of children. In case of overdose, get medical help or contact a Poison Control Center (1-800-222-1222) right away.

Uses

Temporarily relieves these symptoms due to hay fever or other upper respiratory allergies:

- runny nose
- sneezing
- itchy, watery eyes
- itching of the nose or throat

Temporarily relieves these symptoms due to the common cold:

- runny nose
- sneezing

Directions

- Take every 4 to 6 hours, or as directed by a doctor.
- Do not exceed recommended dose.

Adults and Children 12 years of age and over | take 10 to 20 mL (2 to 4 tsp) not to exceed 300 mg in 24 hours
Children 6 to under 12 years of age Children under 6 years of age: | take 5 to 10 mL (1 to 2 tsp) not to exceed 150 mg in 24 hours; consult a doctor

Other Information

- Store at controlled room temperature 15º - 30ºC (59º - 86ºF).
- Do not refrigerate. Avoid excessive heat or humidity.
- Protect from light.

Inactive Ingredients

Citric acid, FD&C red #40, glycerin, methylparaben, propylene glycol, propylparaben, purified water, sodium citrate, sorbitol, strawberry flavor, sucralose.

TAMPER EVIDENT: DO NOT USE IF SEAL UNDER CAP IS TORN, BROKEN OR MISSING.